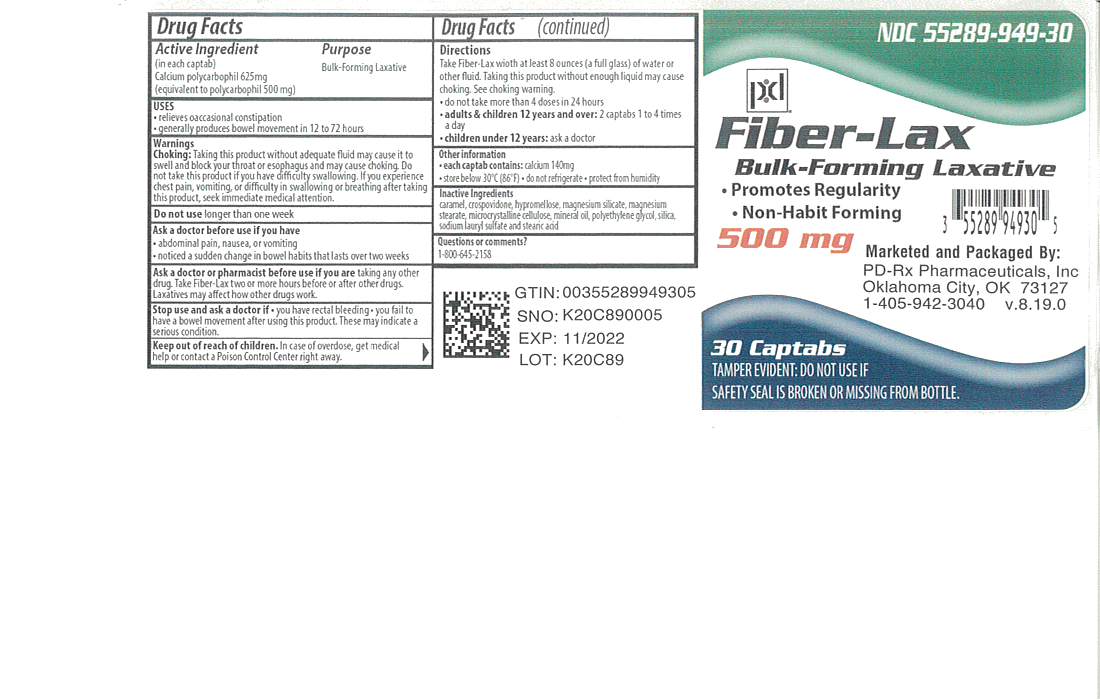 DRUG LABEL: Fiber Lax
NDC: 55289-949 | Form: TABLET, FILM COATED
Manufacturer: PD-Rx Pharmaceuticals, Inc.
Category: otc | Type: HUMAN OTC DRUG LABEL
Date: 20251020

ACTIVE INGREDIENTS: CALCIUM POLYCARBOPHIL 625 mg/1 1
INACTIVE INGREDIENTS: CARAMEL; CROSPOVIDONE, UNSPECIFIED; HYPROMELLOSES; TALC; MAGNESIUM STEARATE; CELLULOSE, MICROCRYSTALLINE; LIGHT MINERAL OIL; POLYETHYLENE GLYCOL 400; SILICON DIOXIDE; SODIUM LAURYL SULFATE; STEARIC ACID

Drug Facts

Active ingredient (in each captab)

Calcium polycarbophil 625 mg

Purpose

Bulk-Forming Laxative

(equivalent to polycarbophil 500 mg)

Uses

- relieves occasional constipation
- generally produces bowel movement in 12 to 72 hours

Warnings

Choking: Taking this product without adequate fluid may cause it to swell and block your throat or esophagus and may cause choking. Do not take this product if you have difficulty in swallowing. If you experience chest pain, vomiting, or difficulty in swallowing or breathing after taking this product, seek immediate medical attention.

Do not use

longer than one week

Ask a doctor before use if you have

- abdominal pain, nausea, or vomiting
- noticed a sudden change in bowel habits that lasts over two weeks

Ask a doctor or pharmacist before use if you are

taking any other drug. Take Fiber-Lax two or more hours before or after other drugs. Laxatives may affect how other drugs work.

Stop use and ask a doctor if

- you have rectal bleeding
- you fail to have a bowel movement after using this product.

These may indicate a serious condition.

Keep out of reach of children.

OVERDOSAGE

In case of overdose, get medical help or contact a Poison Control Center right away.

Directions

Take Fiber-Lax with at least 8 ounces (a full glass) of water or other fluid. Taking this product without enough liquid may cause choking. See choking warning.

- do not take more than 4 doses in 24 hours
- adults & children 12 years and over: 2 captabs 1 to 4 times a day
- children under 12 years: ask a doctor

Other information

- each captab contains: calcium 140 mg
- store below 30˚C (86˚F) • do not refrigerate • protect from humidity

Inactive ingredients

Caramel, crospovidone, hypromellose, magnesium silicate, magnesium stearate, microcrystalline cellulose, mineral oil, polyethylene glycol, silica, sodium lauryl sulfate and stearic acid

Questions or comments?

Call 1-800-645-2158

TAMPER EVIDENT: DO NOT USE IF BLISTER SEAL IS BROKEN OR DAMAGED

*Rugby Laboratories, Inc. is not affiliated with the owner of the trademark FiberCon®.

Distributed by: Rugby Laboratories

17177 N Laurel Park Drive, Suite 233

Livonia, MI 48152

www. Rugbylaboratories.com

16 HOW SUPPLIED

Fiber-Lax Tablets are available as follows:

500 mg: Off White, oval, scored tablet, debossed “CPC 339”. Available in bottles of

30 captabs (NDC 55289-949-30)

PACKAGE LABEL

Fiber-Lax